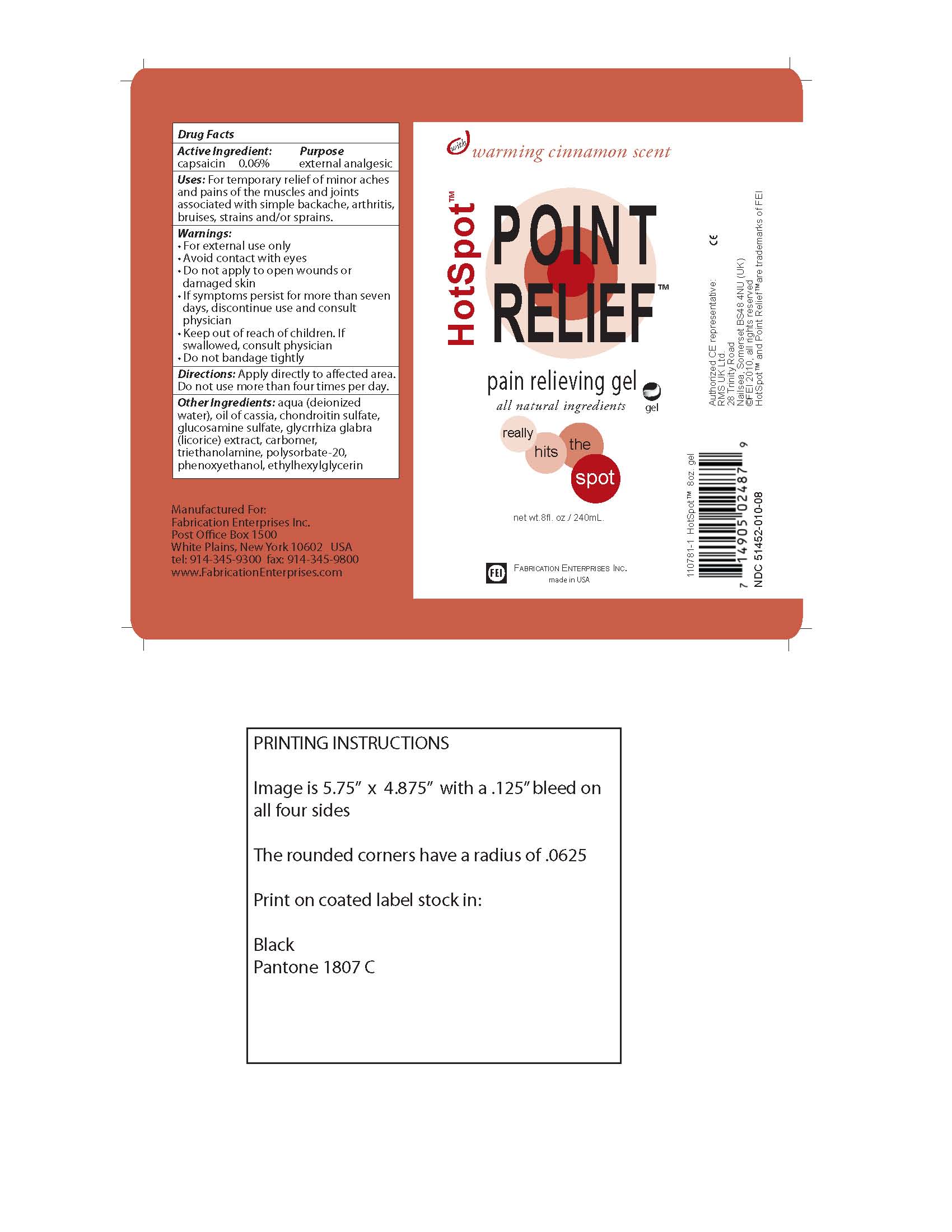 DRUG LABEL: Hot Spot
NDC: 51452-010 | Form: GEL
Manufacturer: fabrication enterprises
Category: otc | Type: HUMAN OTC DRUG LABEL
Date: 20101005

ACTIVE INGREDIENTS: CAPSAICIN 1.5 mL/240 mL
INACTIVE INGREDIENTS: water; polysorbate 20; CHONDROITIN SULFATE (BOVINE); Glucosamine sulfate; GLYCYRRHIZA GLABRA; CARBOMER 1342; PHENOXYETHANOL

Hot Spot Point Relief Pain relieving gel - 8 oz.

Active Ingredients: Capsaicin

INACTIVE INGREDIENT

Inactive Ingredients: deionized water, oil of Cassia, chondroitin sulfate, glucosamine sulfate,Glycrrhiza Glabra (licorice) extract, Carbomer, Triethanolamine, polysorbate-20, Phenoxyethanol, Ethylhexylglycrine.

Keep out of reach of children. If swallowed consult physician

WARNINGS

Warnings Section: For external use only, avoid contact with eyes, do not apply to open wounds or damaged skin, if symptoms persist for more than seven days discontinue use and consult physician, keep out of reach of children and if swallowed consult physician, do not bandage tightly.

PURPOSE

Pain relieving gel

INDICATIONS AND USAGE

Use: For temporary relief of minor aches and pains of the muscles and joints associated with simple backache, arthritis, bruises, strains and/or sprains.

DOSAGE AND ADMINISTRATION

Apply directly to effected area. Do not use more than four times per day.

PACKAGE LABEL

HotSpot Point Relief Pain Relieving gel, all natural ingredients.